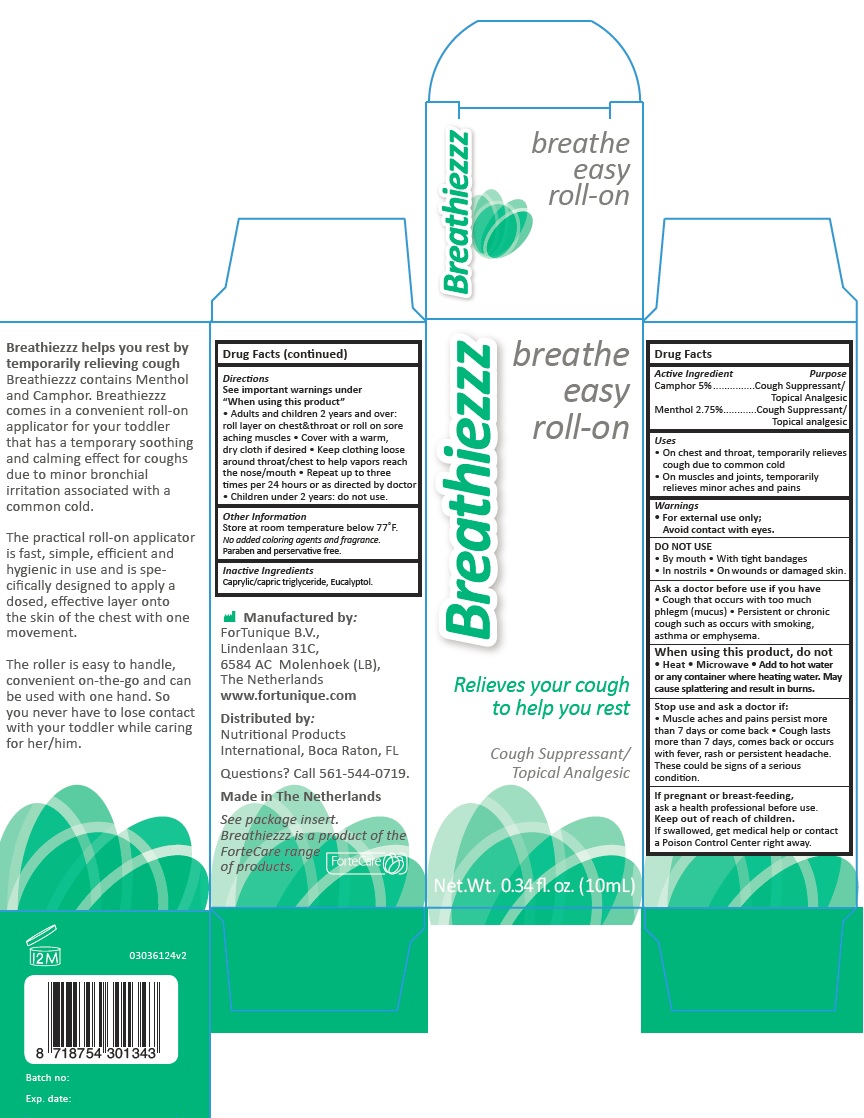 DRUG LABEL: Breathiezzz
NDC: 70359-4107 | Form: OIL
Manufacturer: Fortunique B.V.
Category: otc | Type: HUMAN OTC DRUG LABEL
Date: 20161214

ACTIVE INGREDIENTS: CAMPHOR (SYNTHETIC) 5 g/100 g; MENTHOL, UNSPECIFIED FORM 2.75 g/100 g
INACTIVE INGREDIENTS: MEDIUM-CHAIN TRIGLYCERIDES; EUCALYPTOL

Active Ingredients

Camphor 5%

Menthol 2.75%

Purpose

Cough Suppressant/Topical Analgesic

Uses

On chest and throat, temporarily relieves coungh due to common cold

On muscles and joints, temporarily relieves minor aches and pains

Warning

For external use only

Avoid contact with eyes

Do not use

By mouth. With tinght bandages

In nostrils. On wounds or damaged skin

Ask a Doctor before use if you have

Cough that occurs with to much phlegm(mucus). Persistent or chronic cough such as occurs within smoking, asthma or emphysema

When using this product, do not

Heat. Microwave. Add to hot water or any container where heating water. May cause splattering and result in burns

Stop use and ask a Doctor if

Muscle aches and pains persist more than 7 days or come back. Cough lasts more than 7 days, comes back occurs with fever, rash or persistent headache .

These could be signs of a serious condition

If pregnant or breast-feeding

Ask a health professional before use.

Keep out of reach of children

If swallowed, get medical help or contact a Poison Control Center right away

Directions

See important warnings under " When using this product"

Adults and children 2 years and over: roll layer on chest & throat or roll on sore aching muscles. Cover with a warm, dry cloth if desired. Keep clothing loose around throat /chest to help vapors reach the nose/mouth. Repeat up to three times per 24 hours or as directed by doctor. Children under 2 years: do not use

Other information

Store at room temperature below 77º F

No added coloring agent and fragrance

Paraben and preservative free

Inactive Ingredients

Caprylic/Capric Triglycerides

Eucalyptol